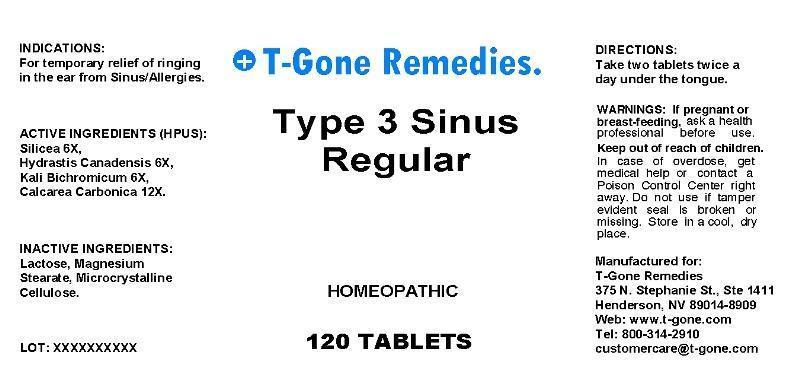 DRUG LABEL: Type 3 Sinus Regular
NDC: 50169-0002 | Form: TABLET, ORALLY DISINTEGRATING
Manufacturer: T Gone Remedies
Category: homeopathic | Type: HUMAN OTC DRUG LABEL
Date: 20130403

ACTIVE INGREDIENTS: SILICON DIOXIDE 6 [hp_X]/1 mg; GOLDENSEAL 6 [hp_X]/1 mg; POTASSIUM DICHROMATE 6 [hp_X]/1 mg; OYSTER SHELL CALCIUM CARBONATE, CRUDE 12 [hp_X]/1 mg
INACTIVE INGREDIENTS: LACTOSE; MAGNESIUM STEARATE; CELLULOSE, MICROCRYSTALLINE

Drug Facts

ACTIVE INGREDIENTS

Silicea 6X, Hydrastis Canadensis 6X, Kali Bichromicum 6X, Calcarea Carbonica 12X

INDICATIONS

For temporary relief of ringing in the ear from Sinus Allergies.

WARNINGS

If pregnant or breast-feeding, ask a health professional before use. Keep out of reach of children. In case of overdose, get medical help or contact a Poison Control Center right away. Do not use if tamper evident seal is broken or missing. Store in a cool, dry place.

DIRECTIONS

Take two tablets twice a day under the tongue.

INACTIVE INGREDIENTS

Lactose, Magnesium Stearate, Microcrystalline Cellulose

KEEP OUT OF REACH OF CHILDREN

In case of overdose, get medical help or contact a Poison Control Center right away.

INDICATIONS AND USAGE

For temporary relief of ringing in the ear from Sinus Allergies.

QUESTIONS

T-Gone Remedies

375 N. Stephanie St., Ste 1411

Henderson, NV 89014-8909

Web: www.t-gone.com

Tel: 800-314-2910

PACKAGE LABEL

T-Gone Remedies

Type 3 Sinus

Regular

120 TABLETS